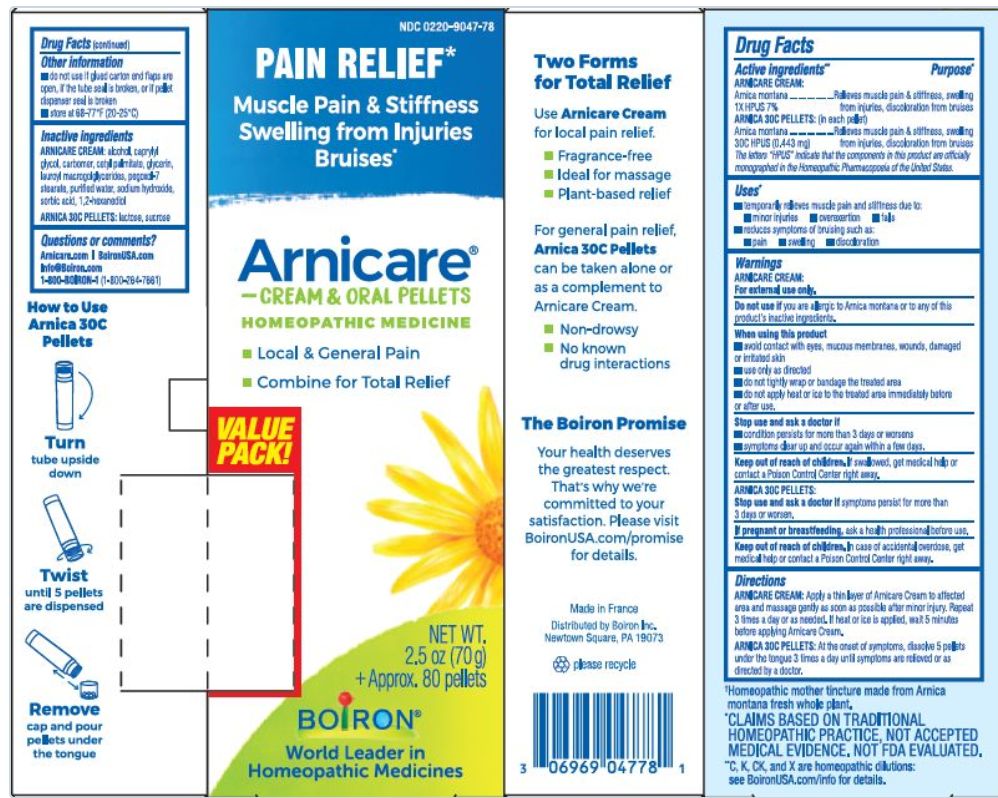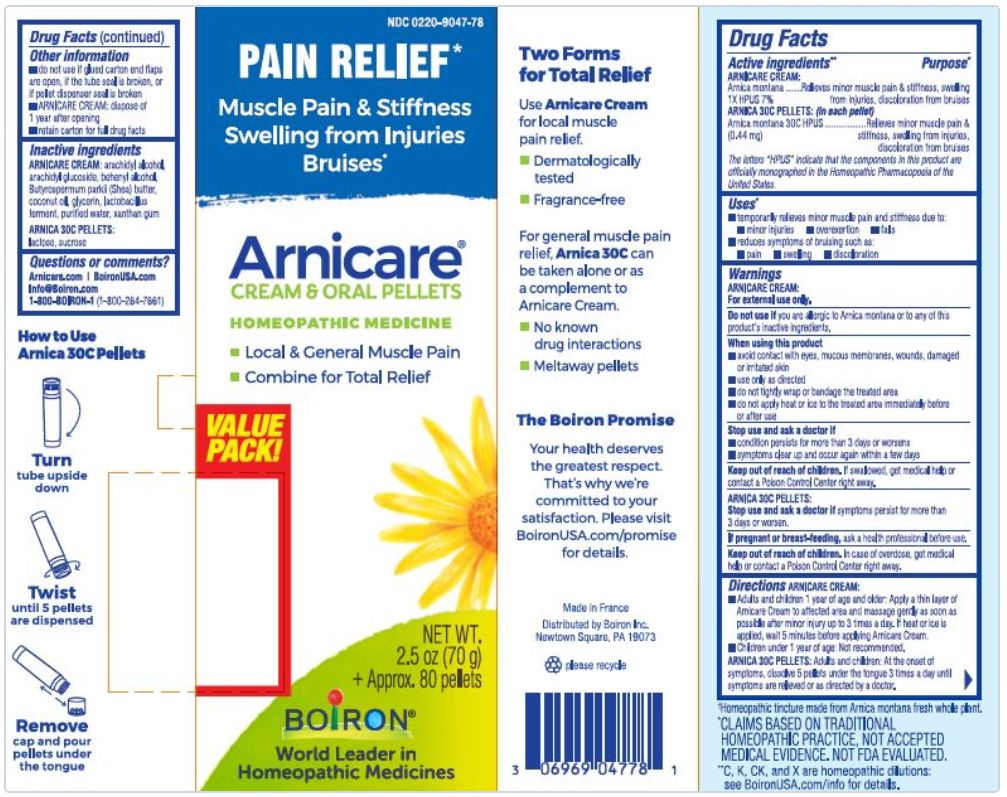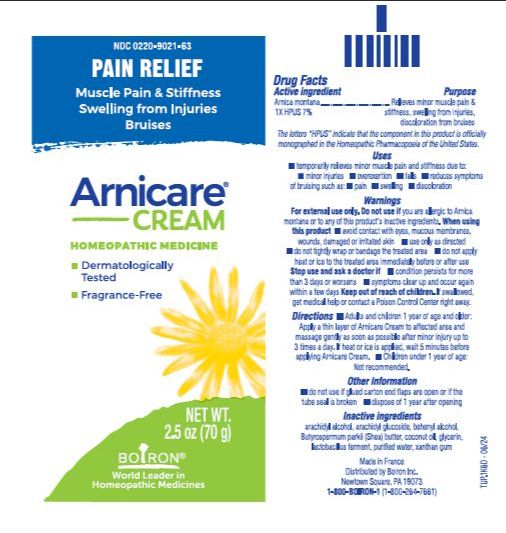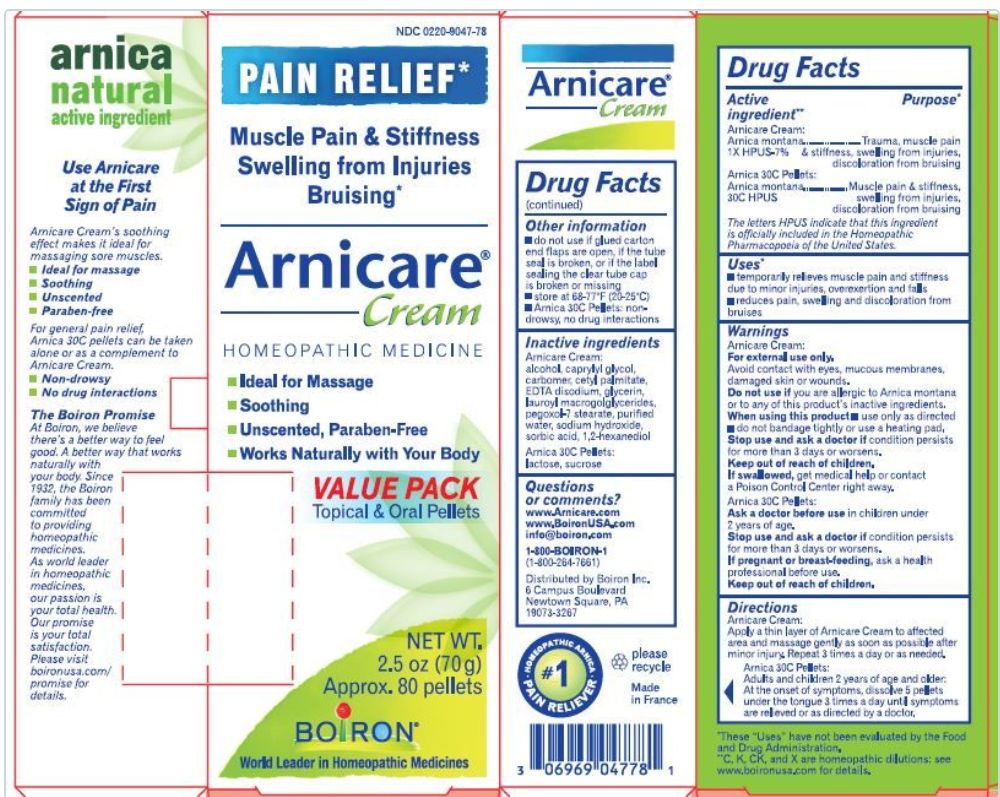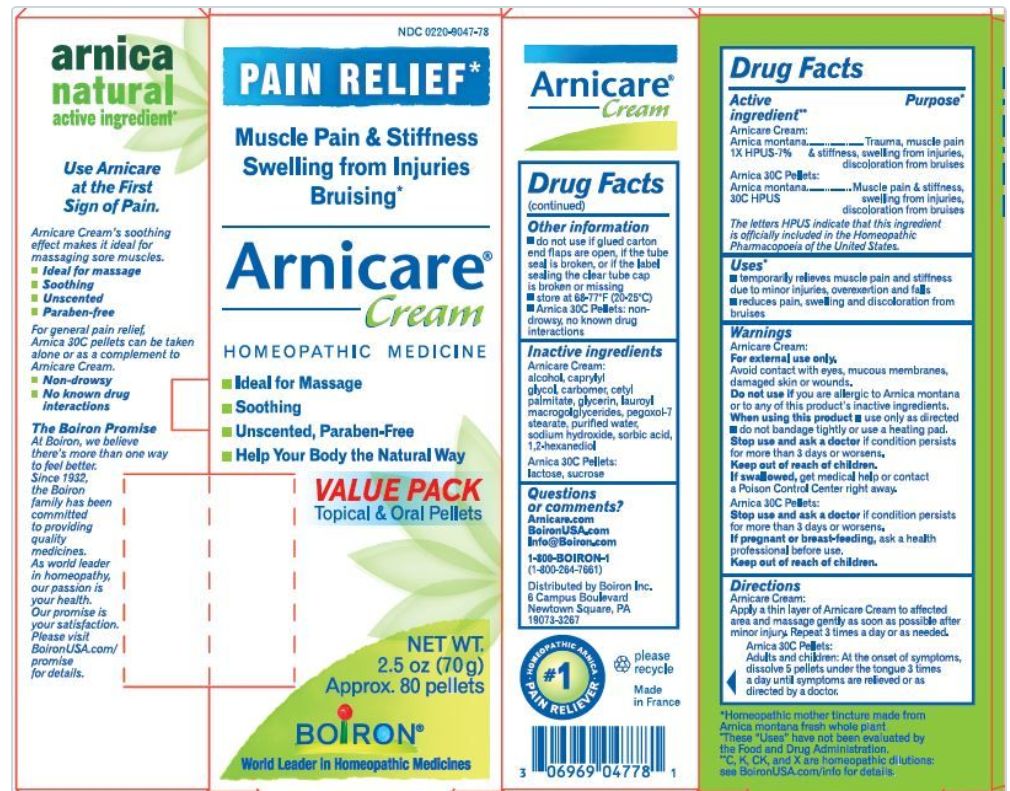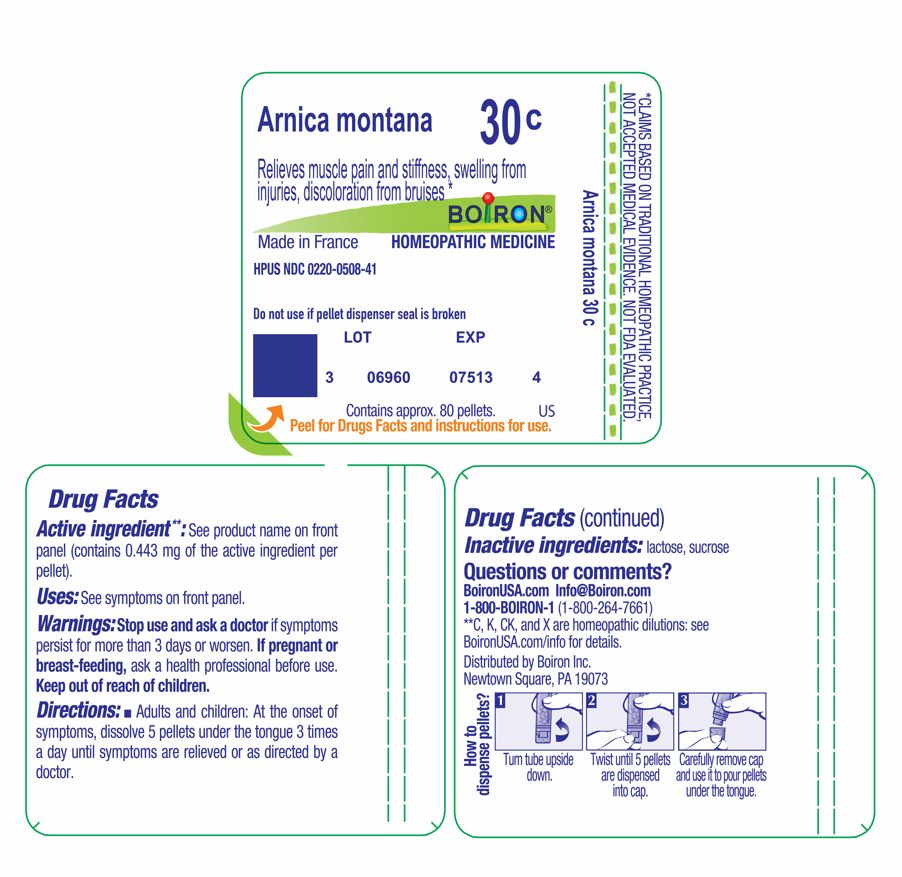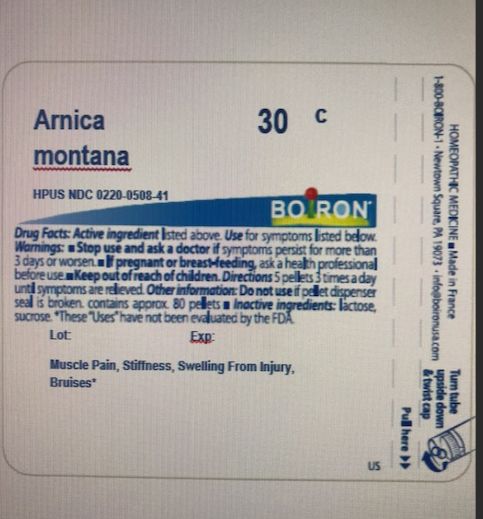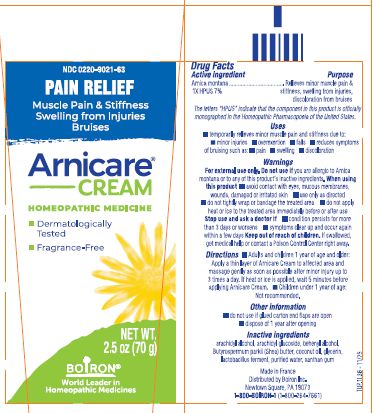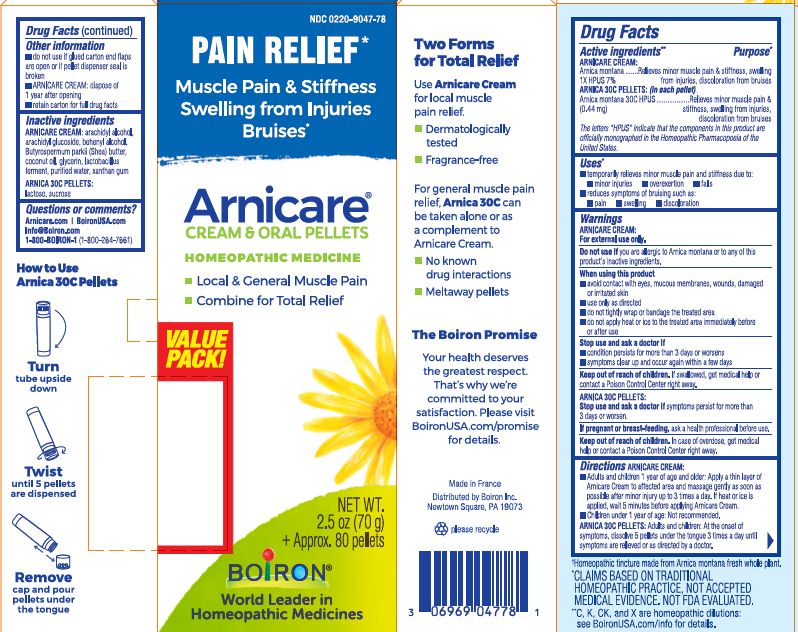 DRUG LABEL: Arnica Value Pack
NDC: 0220-9047 | Form: KIT | Route: ORAL
Manufacturer: Laboratoires Boiron
Category: homeopathic | Type: HUMAN OTC DRUG LABEL
Date: 20251215

ACTIVE INGREDIENTS: ARNICA MONTANA 30 [hp_C]/1 1; ARNICA MONTANA 1 [hp_X]/1 g
INACTIVE INGREDIENTS: SUCROSE; LACTOSE; GLYCERIN; ARACHIDYL ALCOHOL; WATER; XANTHAN GUM; BUTYROSPERMUM PARKII (SHEA) BUTTER UNSAPONIFIABLES; DOCOSANOL; LIMOSILACTOBACILLUS FERMENTUM; ARACHIDYL GLUCOSIDE; COCONUT OIL

Arnicare Cream Value Pack

Active ingredients**

Arnicare Cream:
Arnica Montana 1X HPUS 7%

Arnica 30C pellets: (in each pellet)
Arnica montana 30C HPUS (0.44 mg)

The letters "HPUS" indicate that the components in this product are officially monographed in the Homeopathic Pharmacopoeia of the United States.

Purpose*

Arnicare Cream: Arnica Montana 1X HPUS 7% Relieves minor muscle pain & stiffness, swelling from injuries, discoloration from bruises

Arnica 30 C pellets: Arnica montana 30C HPUS (0.44 mg) Relieves minor muscle pain & stiffness, swelling from injuries, discoloration from bruises

Uses*

- temporarily relieves minor muscle pain and stiffness due to:
- minor injuries
- overexertion
- falls
- reduces symptoms of bruising such as:
- pain
- swelling
- discoloration

WARNINGS

Arnicare Cream:

For external use only.

Do not use if you are allergic to Arnica montana or to any of this product's inactive ingredients.

When using this product

- avoid contact with eyes, mucous membranes, wounds, damaged or irritated skin
- use only as directed
- do not tightly wrap or bandage the treated area
- do not apply heat or ice to the treated area before or after use

Stop use and ask a doctor if

- condition persists for more than 3 days or worsens
- symptoms clear up and occur again within a few days

ARNICA 30 PELLETS:

Stop use and ask a doctor if symptoms persists for more than 3 days or worsen.

Keep out of reach of children. If swallowed, get medical help or contact a Poison Control Center right away.

PREGNANCY OR BREAST FEEDING

If pregnant or breast-feeding, ask a health professional before use.

DOSAGE AND ADMINISTRATION

ARNICARE CREAM:

- Adults and children 1 year of age and older: Apply a thin layer of Arnicare Cream to affected area and massage gently as soon as possible after minor injury up to 3 times a day. If heat or ice is applied, wait 5 minutes before applying Arnicare Cream.
- Children under 1 year of age: Not recommended.

ARNICA 30C PELLETS:

Adults and children: At the onset of symptoms, dissolve 5 pellets under the tongue 3 times a day until symptoms are relieved or as directed by a doctor.

INACTIVE INGREDIENT

ARNICARE CREAM: arachidyl alcohol, arachidyl glucoside, behenyl alcohol, Butyrospermum parkii (Shea) butter, coconut oil, glycerin, lactobacillus ferment, purified water, xanthan gum

ARNICA 30C PELLETS: lactose, sucrose

QUESTIONS

Arnicare.com

BoironUSA.com

Info@Boiron.com

1-800-BOIRON-1

(1-800-264-7661)

Distributed by Boiron Inc.

Newtown Square, PA 19073

do not use if glued end flaps are open or if pellet dispenser seal is broken

ARNICARE CREAM: dispose of 1 year after opening

retain carton for full drug facts

How to use Arnica 30C Pellets Turn tube upside down Twist until 5 pellets are dispensed Remove cap and pour pellets under tongue

2.5 oz (70 g)

+ Approx. 80 pellets

meltaway pellets

Pain Relief*

Muscle Pain & Stiffness Swelling from Injuries Bruises*

Local & General Muscle Pain

No known drug interactions

ɨ Homeopathic mother tincture made from Arnica montana fresh whole plant.

*CLAIMS BASED ON TRADITIONAL HOMEOPATHIC PRACTICE NOT ACCEPTED MEDICAL EVIDENCE. NOT FDA EVALUATED.
**C,K,CK, and X are homeopathic dilutions: see BoironUSA.com/info for details.